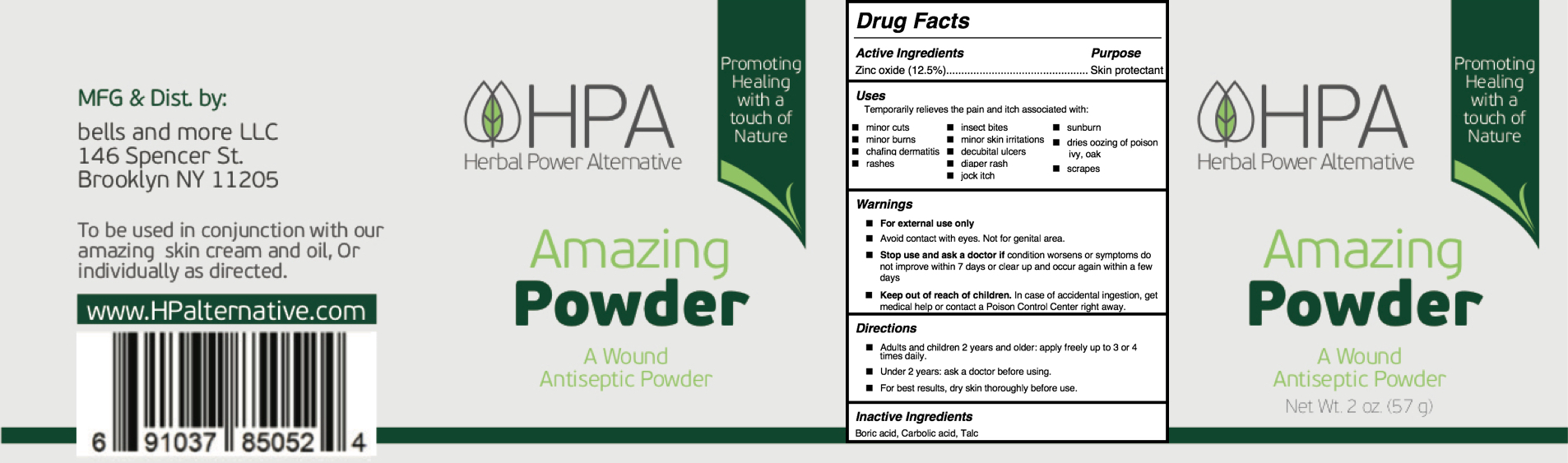 DRUG LABEL: Herbal Power Alternative
NDC: 81386-003 | Form: POWDER
Manufacturer: BELLS & MORE INC
Category: otc | Type: HUMAN OTC DRUG LABEL
Date: 20210316

ACTIVE INGREDIENTS: ZINC OXIDE 12.5 g/100 g
INACTIVE INGREDIENTS: PHENOL; TALC; BORIC ACID

HPA Antiseptic Powder

Active Ingredients

Zinc oxide (12.5%)

Purpose

Skin protectant

Uses

Dries oozing of poison ivy, oak, and temporarily relieves the pain and itch associated with:

- minor skin irritations, cuts, scrapes, burns
- insect bites, rashes, jock itch
- sunburn, diaper rash, chafing dermatitis
- decubital ulcers

Warnings

- For external use only
- Avoid contact with eyes. Not for genital area.

Stop use and ask a doctor if condition worsens or symptoms do not improve within 7 days or clear up and occur again within a few days

Keep out of reach of children. In case of accidental ingestion, get medical help or contact a Poison Control Center right away.

Directions

- Adults and children 2 years and older: apply freely up to 3 or 4 times daily.
- Under 2 years: ask a doctor before using.
- For best results, dry skin thoroughly before use.

Inactive Ingredients

Boric acid, Carbolic acid, Talc

Principal Display Panel

57 g NDC: 81386-003-57